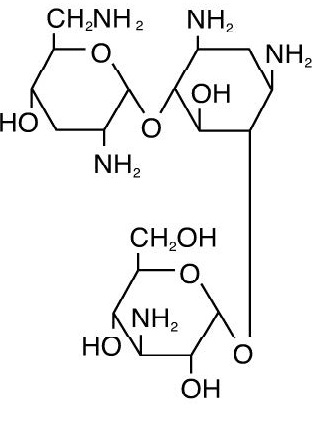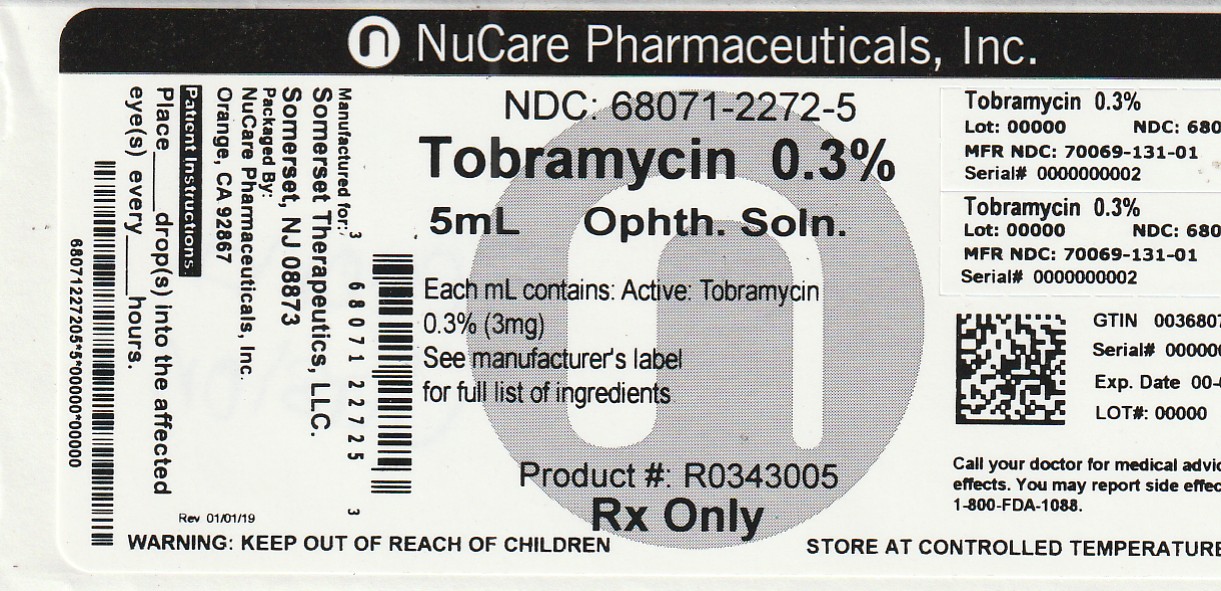 DRUG LABEL: Tobramycin
NDC: 68071-2272 | Form: SOLUTION/ DROPS
Manufacturer: NuCare Pharmaceuticals,Inc.
Category: prescription | Type: HUMAN PRESCRIPTION DRUG LABEL
Date: 20260204

ACTIVE INGREDIENTS: TOBRAMYCIN 3 mg/1 mL
INACTIVE INGREDIENTS: BENZALKONIUM CHLORIDE; BORIC ACID; SODIUM SULFATE ANHYDROUS; TYLOXAPOL; SODIUM CHLORIDE; SODIUM HYDROXIDE; SULFURIC ACID; WATER

Rx Only
For Topical Ophthalmic Use Only

DESCRIPTION

Tobramycin ophthalmic solution is a sterile topical ophthalmic antibiotic formulation prepared specifically for topical therapy of external ophthalmic infections.

Each mL of Tobramycin ophthalmic solution USP, 0.3% contains: Active: tobramycin 0.3% (3 mg). Preservative: Benzalkonium chloride 0.01% (0.1 mg). Inactives: boric acid, sodium sulfate, sodium chloride, tyloxapol, sodium hydroxide and/or sulfuric acid (to adjust pH) and water for injection. Tobramycin ophthalmic solution has a pH range between 7.0 and 8.0 and an osmolality of 260-320 mOsm/kg.

Tobramycin is a water-soluble aminoglycoside antibiotic active against a wide variety of gram-negative and gram-positive ophthalmic pathogens.

The chemical structure of tobramycin is:

Molecular Weight = 467.52

Molecular Formula: C18H37N5O9

Chemical name: 0-{3-amino-3-deoxy-α-D-gluco-pyranosyl-(1→4) }-0-{2,6-diamino-2,3,6-trideoxy-α-D-ribohexo-pyranosyl-(1→6) }-2-deoxystreptamine.

CLINICAL PHARMACOLOGY

In Vitro Data: In vitro studies have demonstrated tobramycin is active against susceptible strains of the following microorganisms: Staphylococci, including S. aureus and S. epidermidis (coagulase-positive and coagulase-negative), including penicillin-resistant strains.

Streptococci, including some of the Group A-beta-hemolytic species, some nonhemolytic species, and some Streptococcus pneumoniae.

Pseudomonas aeruginosa, Escherichia coli, Klebsiella pneumoniae, Enterobacter aerogenes, Proteus mirabilis, Morganella morganii, most Proteus vulgaris strains, Haemophilus influenzae and H. aegyptius, Moraxella lacunata, Acinetobacter calcoaceticus and some Neisseria species. Bacterial susceptibility studies demonstrate that in some cases, microorganisms resistant to gentamicin retain susceptibility to tobramycin.

INDICATIONS AND USAGE

Tobramycin ophthalmic solution is a topical antibiotic indicated in the treatment of external infections of the eye and its adnexa caused by susceptible bacteria. Appropriate monitoring of bacterial response to topical antibiotic therapy should accompany the use of Tobramycin Ophthalmic Solution. Clinical studies have shown tobramycin to be safe and effective for use in children.

CONTRAINDICATIONS

Tobramycin ophthalmic solution is contraindicated in patients with known hyper sensitivity to any of its components.

WARNINGS

FOR TOPICAL OPHTHALMIC USE ONLY. NOT FOR INJECTION INTO THE EYE. Sensitivity to topically applied aminoglycosides may occur in some patients. If a sensitivity reaction to Tobramycin ophthalmic solution occurs, discontinue use.

PRECAUTIONS

General

As with other antibiotic preparations, prolonged use may result in overgrowth of nonsusceptible organisms, including fungi. If superinfection occurs, appropriate therapy should be initiated. Cross-sensitivity to other aminoglycoside antibiotics may occur; if hypersensitivity develops with this product, discontinue use and institute appropriate therapy. Patients should be advised not to wear contact lenses if they have signs and symptoms of bacterial ocular infection.

Information For Patients

Do not touch dropper tip to any surface, as this may contaminate the solution.

Pregnancy Category B

Reproduction studies in three types of animals at doses up to thirty-three times the normal human systemic dose have revealed no evidence of impaired fertility or harm to the fetus due to tobramycin. There are, however, no adequate and well-controlled studies in pregnant women. Because animal studies are not always predictive of human response, this drug should be used during pregnancy only if clearly needed.

Nursing Mothers

Because of the potential for adverse reactions in nursing infants from Tobramycin ophthalmic solution, a decision should be made whether to discontinue nursing the infant or discontinue the drug, taking into account the importance of the drug to the mother.

Pediatric Use

Safety and effectiveness in pediatric patients below the age of 2 months has not been established.

Geriatric Use

No overall differences in safety or effectiveness have been observed between elderly and younger patients.

ADVERSE REACTIONS

The most frequent adverse reactions to Tobramycin ophthalmic solution are hypersensitivity and localized ocular toxicity, including lid itching and swelling, and conjunctival erythema. These reactions occur in less than three of 100 patients treated with Tobramycin ophthalmic solution. Similar reactions may occur with the topical use of other aminoglycoside antibiotics. Other adverse reactions have not been reported from Tobramycin ophthalmic solution therapy; however, if topical ocular tobramycin is administered concomitantly with systemic aminoglycoside antibiotics, care should be taken to monitor the total serum concentration.

OVERDOSAGE

Clinically apparent signs and symptoms of an overdose of Tobramycin ophthalmic solution (punctate keratitis, erythema, increased lacrimation, edema and lid itching) may be similar to adverse reaction effects seen in some patients.

DOSAGE AND ADMINISTRATION

In mild to moderate disease, instill one or two drops into the affected eye(s) every four hours. In severe infections, instill two drops into the eye(s) hourly until improvement, following which treatment should be reduced prior to discontinuation.

HOW SUPPLIED

5 mL sterile solution is packaged in a 10 mL white LDPE bottle and natural LDPE nozzle and White HDPE cap (NDC 68071-2272-5) containing Tobramycin ophthalmic solution.

TAMPER EVIDENT SEAL

Storage: Store at 2° - 25°C (36° - 77°F).

For Product Inquiry call +1-800-417-9175

Revised: October, 2019

Manufactured for:

Somerset Therapeutics, LLC

Hollywood, FL 33024

Made in India

Code No.: KR/DRUGS/KTK/28/289/97

ST-TBR11/P/03